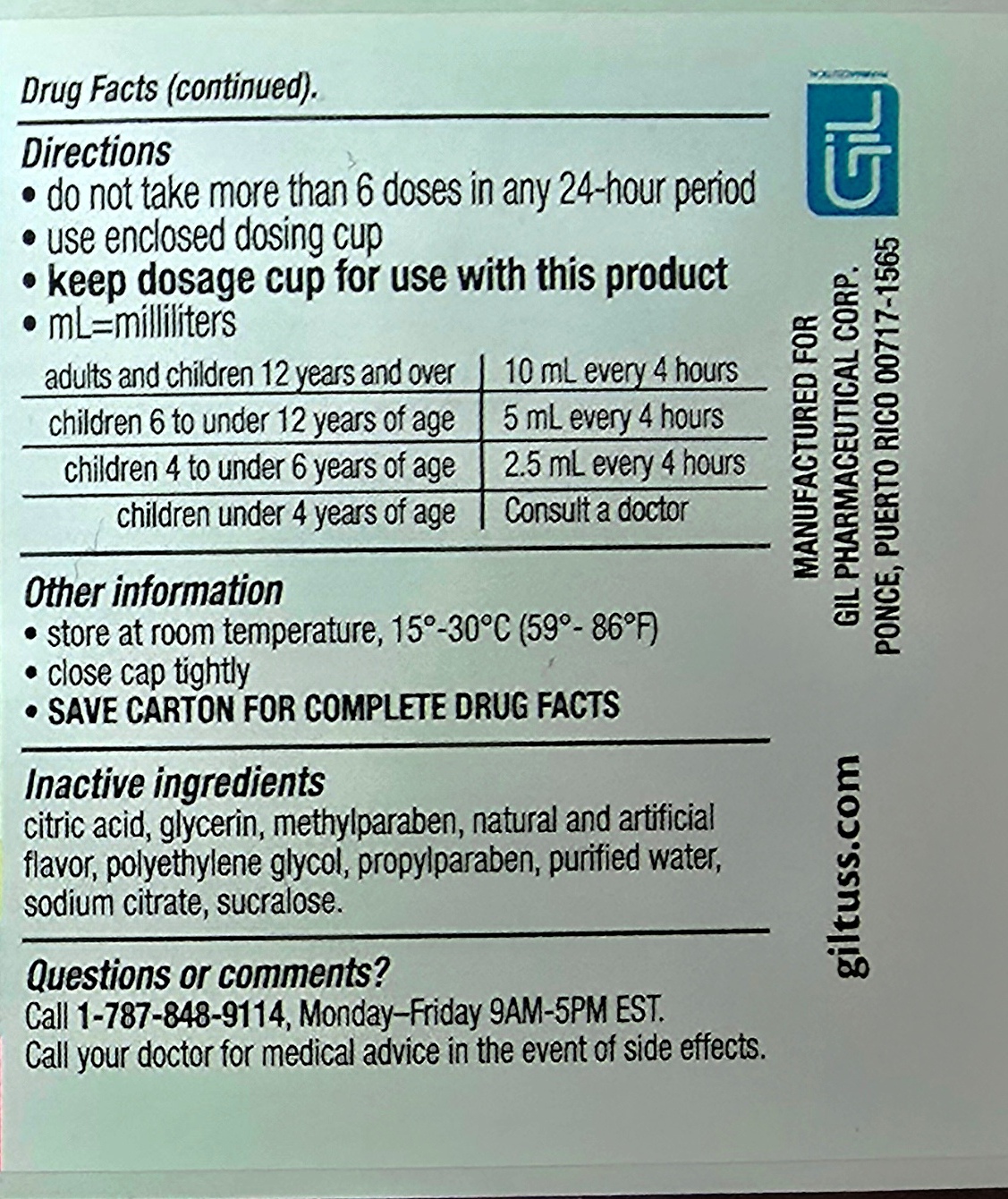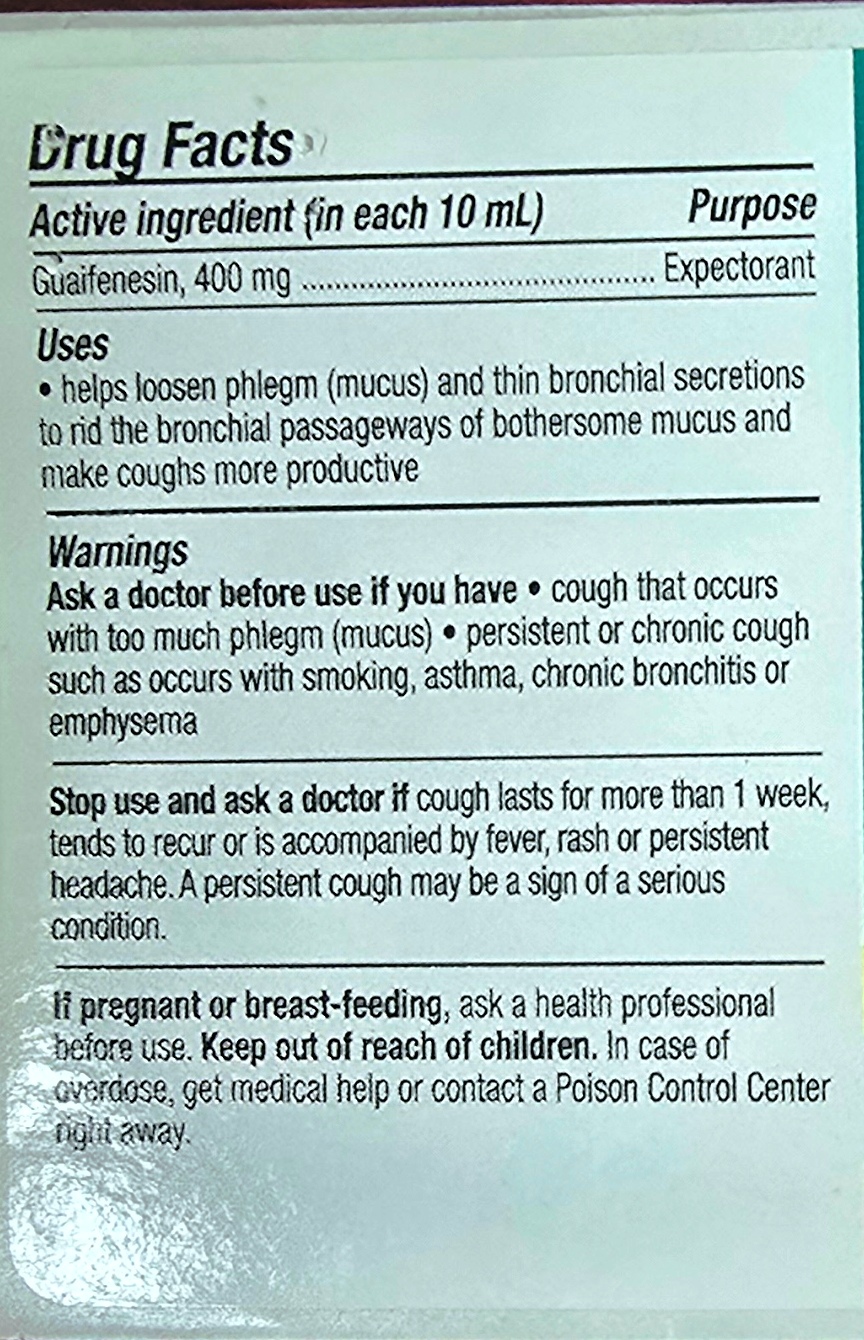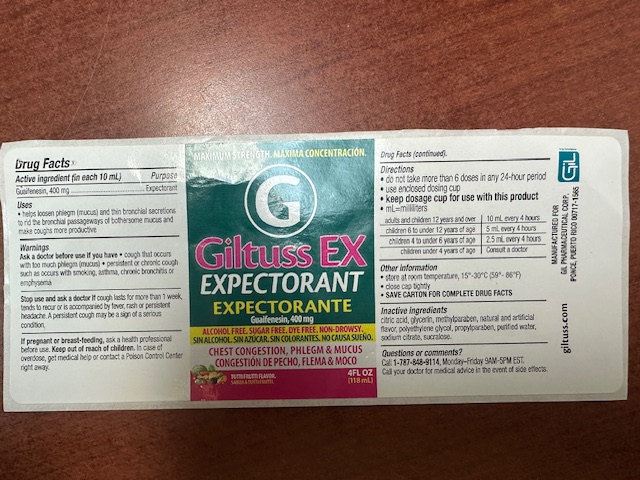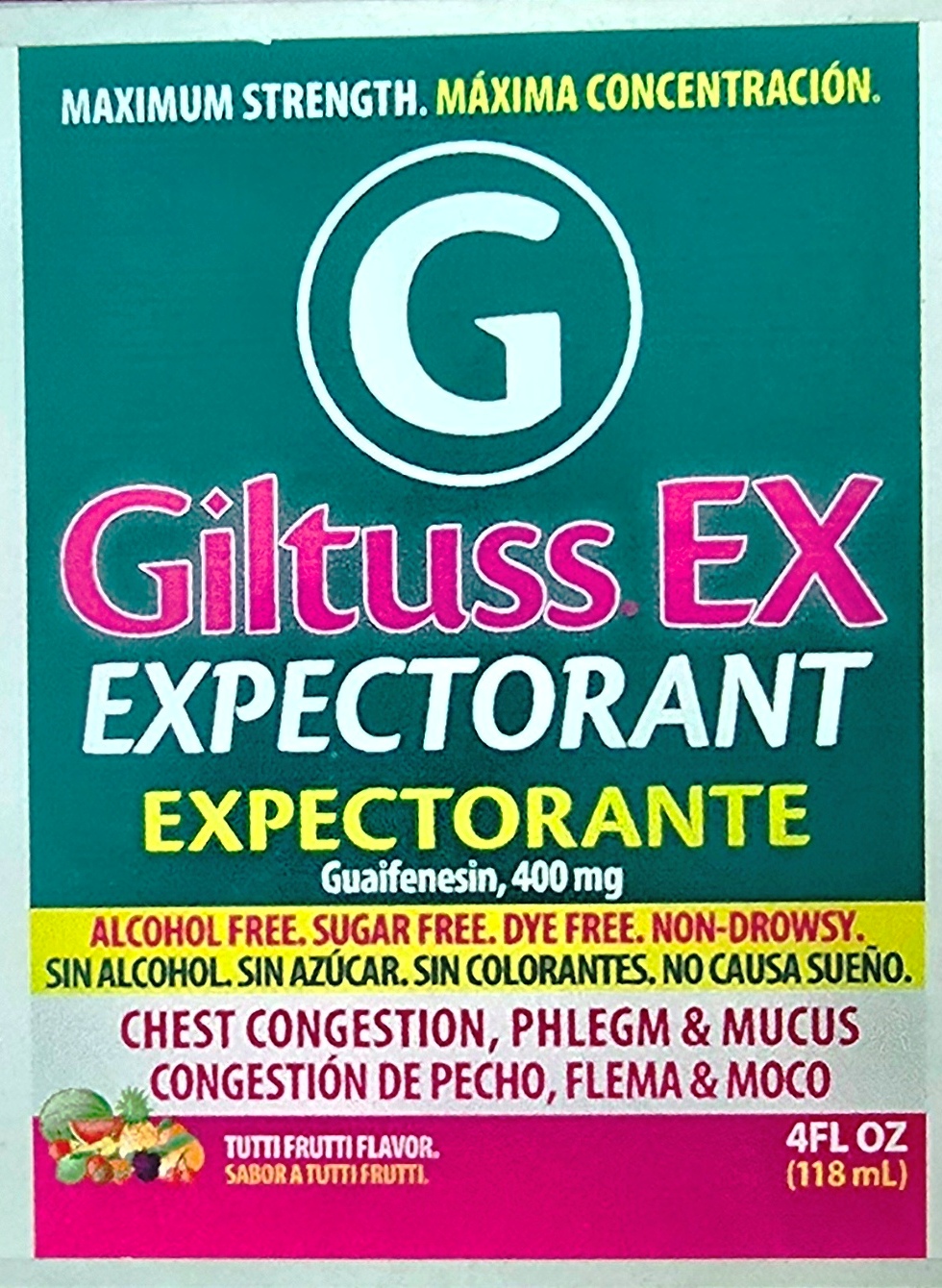 DRUG LABEL: Giltuss EX Expectorant
NDC: 65852-008 | Form: SOLUTION
Manufacturer: Dextrum Laboratories Inc.
Category: otc | Type: HUMAN OTC DRUG LABEL
Date: 20250922

ACTIVE INGREDIENTS: GUAIFENESIN 400 mg/10 mL
INACTIVE INGREDIENTS: SUCRALOSE; WATER; CITRIC ACID; SODIUM CITRATE; PROPYLPARABEN; GLYCERIN; METHYLPARABEN; PROPYLENE GLYCOL

Giltuss EX Expectorant

Active Ingredients

Guafenesin, 400 mg

Uses

Purpose

Expectorant

Uses

- helps loosen phlegm (mucus) and thin bronchial secretions to rid the bronchial passageway of bothersome mucus and make coughs more productive

Warnings

- Ask a doctor before use if you have , cough that occurs with too much phlegm (mucus) , persistent or chronic cough such occurs with smoking, asthma, or chronic bronchitis or emphysema

Stop Use

Stop use and ask a doctor if cough lasts for more than 1 week, tends to recur or is accompanied by fever, rash or persistent headache. A persistant cough may be a sign of a serious condition

If pregnant or breast- feeding, ask a health professional before use. Keep out of reach of children. In case of accidental overdose, get medical or professional help or contact a Poisson Control center immediately

Directions

Do not take more than 6 doses in any 24 hours period

Use enclosed dosing cup

Keep dosing cup for use this product

ml= mililiters

Adults and children 12 years & over 10 ml every 4 hours

children 6 to under 12 years of age 5 ml every 4 hours

children 4 to under 6 years of age 2.5 ml every 4 hours

children under 4 years of age Consult a doctor

Other information

Store at room temperature 15-30 °C (59° -86 ° F)
Close cap tightly
SAVE CARTON FOR COMPLETE DRUG FACTS

Inactive Ingredients

Citric acid, glycerin, methylparaben,natural and artificial flavor, polyethylene glycol, propylparaben, purified water, sodium citrate, sucralose

Questions and comments

Call 1-787-848-9114, Monday-Friday 9AM-5PM EST

call your doctor for medical advice in the event of side effects

Indication and user section

Indication and usage

Do not take more than 6 doses in any 24- hours period.

Keep sosage cup for use with this product

Adults and children 12 years and over 10 ml every 4 hours

Children 6 to under 12 years of age 5ml every 4 hours

Children 4 to under 6 years of age 2.5ml ever 4 hours

Children under 4 years of age Consult a doctor

Keep out of reach of children

In case of accidental overdose, get medical or professional help or contact a Poison Control center immediately

PACKAGE LABEL

Maximun strength Giltuss EX Expectorant

Guafenesin 400 mg

Alcohol free, sugar free, Dye free, Non-Drowsy

Chest congestion, Phlegm & Mucus

Tutti Frutti Flavor

4 floz 118 ml